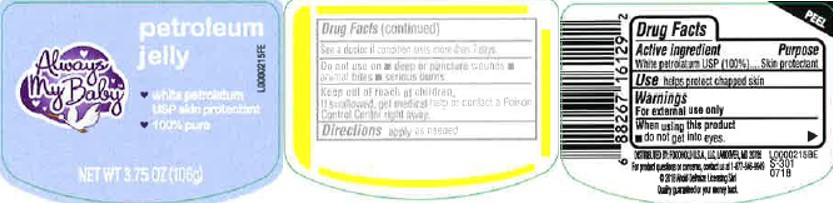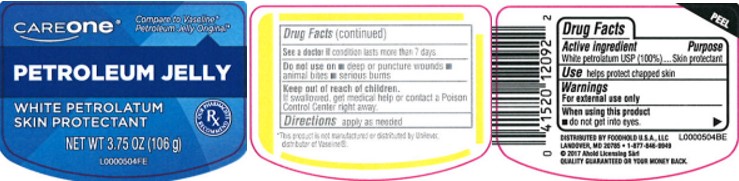 DRUG LABEL: Petrolatum
NDC: 72476-069 | Form: JELLY
Manufacturer: Retail Business Services, LLC
Category: otc | Type: HUMAN OTC DRUG LABEL
Date: 20260206

ACTIVE INGREDIENTS: PETROLATUM 1 g/1 g

Care One_Always My Baby 069.001/069AA
Petroleum Jelly

Active ingredients

White petrolatum USP (100%)

purpose

Skin Protectant

Use

- helps protect chapped skin

Warnings

For external use only

When using this product

- do not get into eyes

See a doctor if

condition lasts more than 7 days

Do not use on

- deep or puncture wounds
- animal bites
- serious burns

Keep out of reach of children

If swallowed, get medical help or contact a Poison Control Center right away.

Directions

apply as needed

INACTIVE INGREDIENT

None

Disclaimer

*This product is not manufactured or distributed by Unilever, distributor of Vaseline.

Adverse Reactions

DISTRIBUTED BY FOODHOLD U.S.A., LLC

LANDOVER, MD 20785 1-877-846-9949

©2017 Ahold Licensing Sarl

QUALITY GUARANTEED OR YOUR MONEY BACK

principal display panel

CAREONE®

Compare to Vaseline® Petroleum Jelly Original*

PETROLEUM JELLY

WHITE PETROLATUM

SKIN PROTECTANT

NET WT 3.75 OZ (106 g)

principal display panel

Always My Baby™

petroleum jelly

- white petroleum USP skin protectant
- 100% Pure

NET WT 3.75 OZ (106 g)